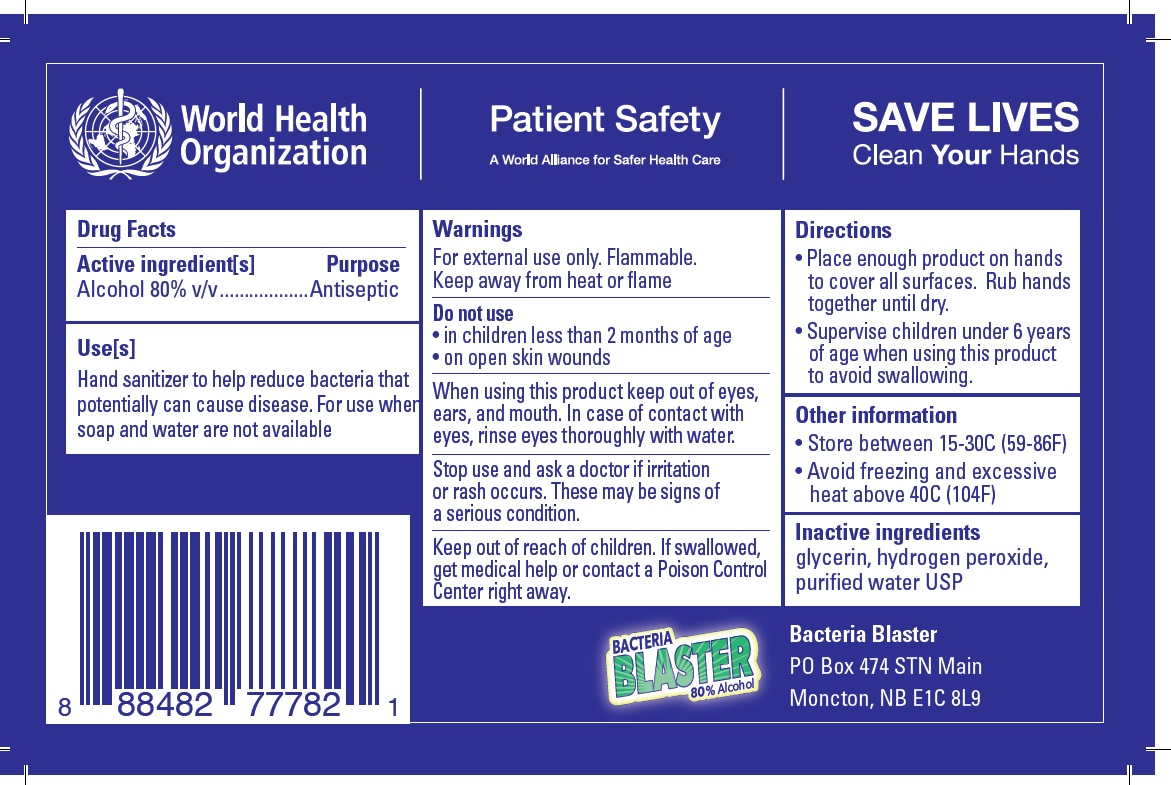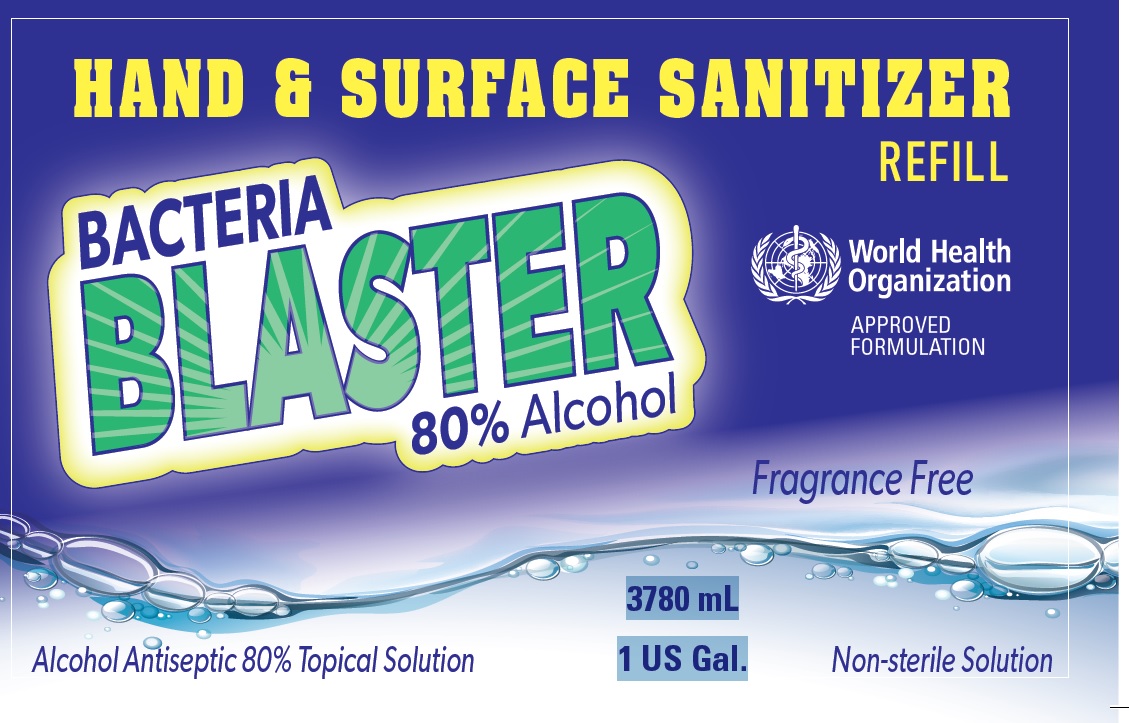 DRUG LABEL: Bacteria Blaster
NDC: 76653-080 | Form: SOLUTION
Manufacturer: Port Royal Distillers Inc.
Category: otc | Type: HUMAN OTC DRUG LABEL
Date: 20200423

ACTIVE INGREDIENTS: ALCOHOL 80 mL/100 mL
INACTIVE INGREDIENTS: GLYCERIN 1.45 L/100 mL; HYDROGEN PEROXIDE 0.125 L/100 mL; WATER 18.425 L/100 mL

Active Ingredient

Alcohol 80% v/v.

Purpose

Antiseptic

Use

Hand Sanitizer to help reduce bacteria that potentially can cause disease. For use when soap and water are not available.

Warnings

For external use only. Flammable. Keep away from heat or flame

Do not use

- in children less than 2 months of age
- on open skin wounds

When using this product

keep out of eyes, ears, and mouth. In case of contact with eyes, rinse eyes thoroughly with water.
Stop use and ask a doctor if irritation or rash occurs. These may be signs of a serious condition.
Keep out of reach of children. If swallowed, get medical help or contact a Poison Control Center right away.

Stop use and ask a doctor if

irritation or rash occurs. These may be signs of a serious condition.

Keep out of reach of children.

If swallowed, get medical help or contact a Poison Control Center right away.

Directions

- Place enough product on hands to cover all surfaces. Rub hands together until dry.
- Supervise children under 6 years of age when using this product to avoid swallowing.

Other information

- Store between 15-30C (59-86F)
- Avoid freezing and excessive heat above 40C (104F)

Inactive ingredients

glycerin, hydrogen peroxide, purified water USP

Principal Display Panel

NDC 76653-080-01

HAND AND SURFACE SANITIZER

REFILL

BACTERIA BLASTER

80% ALCOHOL

WORLD HEALTH ORGANIZATION APPROVED FORMULA

Fragrance Free

Alcohol Antiseptic 80% Topical Solution

Non-sterile Solution

3780 mL

1 US Gal.